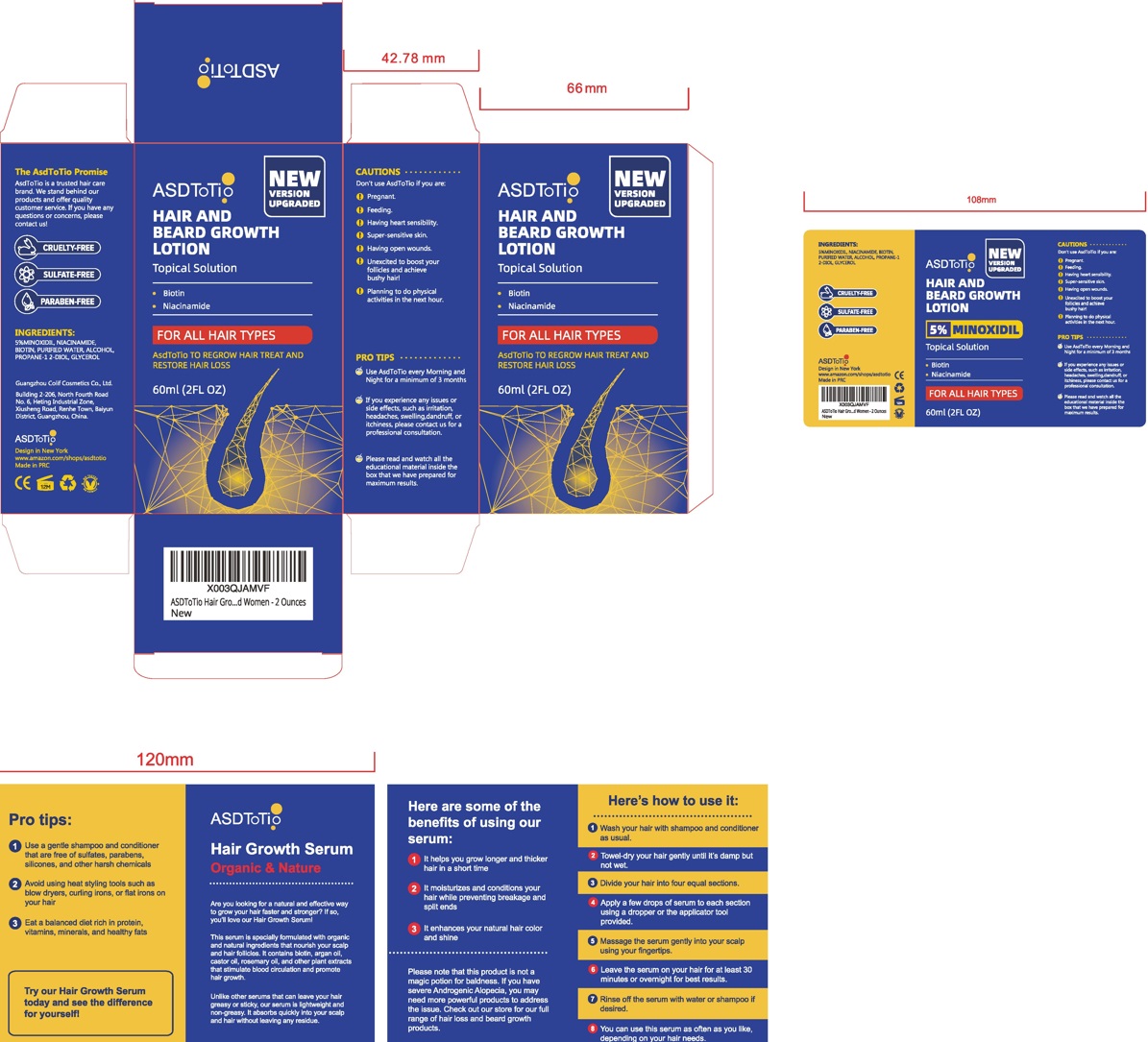 DRUG LABEL: ASDTOTIO 5% minoxidil
NDC: 83870-001 | Form: LIQUID
Manufacturer: Guangzhou Colif Cosmetics Co., Ltd.
Category: otc | Type: HUMAN OTC DRUG LABEL
Date: 20231222

ACTIVE INGREDIENTS: MINOXIDIL 5 g/100 mL
INACTIVE INGREDIENTS: NIACINAMIDE; PROPYLENE GLYCOL; WATER; BIOTIN; ALCOHOL

83870-001

Active ingredient

Minoxidil 5% w/v

Purpose

Promotes hair growth

Use

Hair growth serum to help firming hair root and balancing the head skin secretion, improve thescalp itching, remove the grease, clear the hair follicles to promote the hair growth, reduce the hair loss and broken hair, give you a healthy hair looks.

Warings

When using this product

keep out of eyes, ears, and mouth. In case of contact with eyes, rinse eyes thoroughly with water.

Stop use and ask a doctor

if irritation or rash occurs. These may be signs of a serious condition.

Dot not use

■ Pregnant women and children.
■ on open skin wounds

Keep out of reach of children.

If swallowed, get medical help or contact a Poison Control Center right away. (1-800-222-1222)

Directions

Put right amount of hair growth serum apply on the hairloss area or hair scalp, gentle to massage to help absort.
1-2 times per day.

Other information

Store between 15-25°C (59-86°F)
Avoid freezing and excessive heat above 40°C (104°F)

lnactive ingredients

abcdeniacinamide, biotin, purified water, alcohol, propane-1 2-diol, glycerol